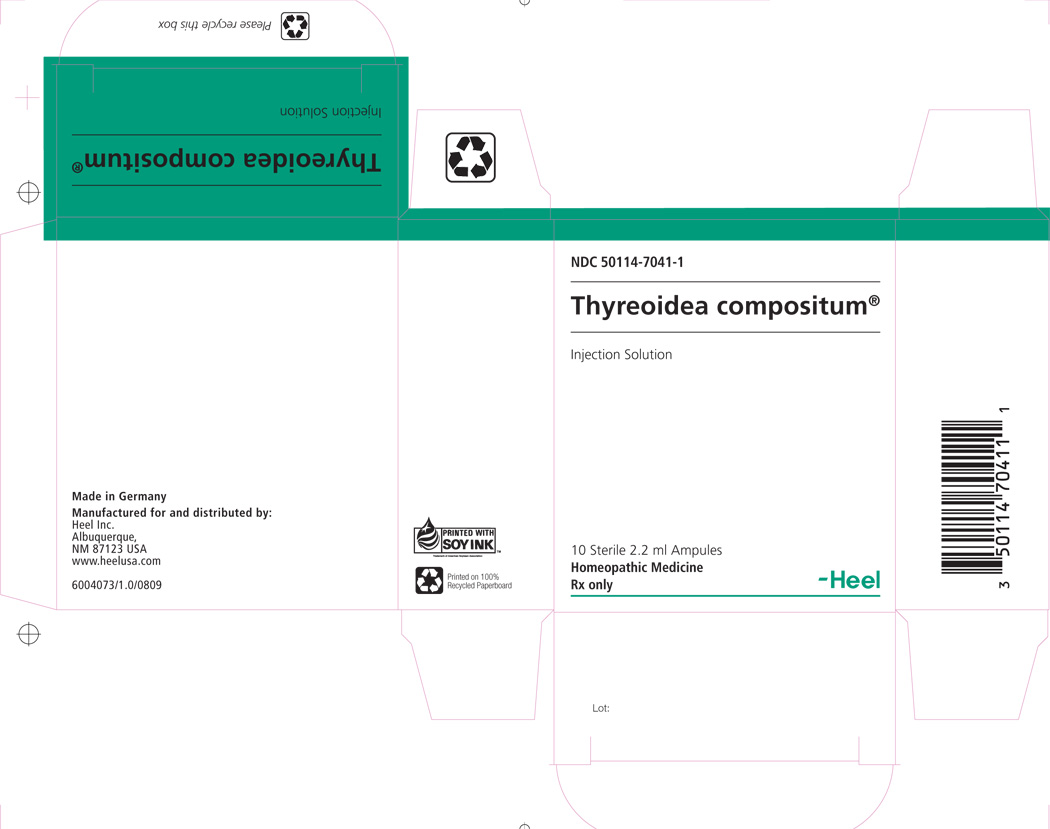 DRUG LABEL: Thyreoidea Compositum
NDC: 50114-7041 | Form: INJECTION
Manufacturer: Heel Inc
Category: homeopathic | Type: HUMAN PRESCRIPTION DRUG LABEL
Date: 20110708

ACTIVE INGREDIENTS: LACTIC ACID, L- 3 [hp_X]/2.2 mL; COLCHICUM AUTUMNALE BULB 4 [hp_X]/2.2 mL; CONIUM MACULATUM FLOWERING TOP 4 [hp_X]/2.2 mL; GALIUM APARINE 4 [hp_X]/2.2 mL; FUCUS VESICULOSUS 6 [hp_X]/2.2 mL; SEDUM ACRE 6 [hp_X]/2.2 mL; SEMPERVIVUM TECTORUM LEAF 6 [hp_X]/2.2 mL; ADENOSINE TRIPHOSPHATE 8 [hp_X]/2.2 mL; FUMARIC ACID 8 [hp_X]/2.2 mL; .ALPHA.-KETOGLUTARIC ACID 8 [hp_X]/2.2 mL; MALIC ACID 8 [hp_X]/2.2 mL; SODIUM DIETHYL OXALACETATE 8 [hp_X]/2.2 mL; PULSATILLA VULGARIS 8 [hp_X]/2.2 mL; SPONGIA OFFICINALIS SKELETON, ROASTED 8 [hp_X]/2.2 mL; SUS SCROFA THYROID 8 [hp_X]/2.2 mL; CALCIUM FLUORIDE 10 [hp_X]/2.2 mL; SUS SCROFA UMBILICAL CORD 10 [hp_X]/2.2 mL; PORK LIVER 10 [hp_X]/2.2 mL; SUS SCROFA BONE MARROW 10 [hp_X]/2.2 mL; SUS SCROFA SPLEEN 10 [hp_X]/2.2 mL; SULFUR 10 [hp_X]/2.2 mL; SUS SCROFA THYMUS 10 [hp_X]/2.2 mL; VISCUM ALBUM FRUIT 3 [hp_X]/2.2 mL; CORTISONE ACETATE 28 [hp_X]/2.2 mL

Thyreoidea Compositum 2.2ml Injection

DESCRIPTION

Injection Solution Ingredient Information: Each 2.2ml ampule contains: Sarcolacticum acidum 3X, Viscum album 3X, Colchicum autumnale 4X, Conium maculatum 4X, Galium aparine 4X, Fucus vesiculosus 6X, Sedum acre 6X, Sempervivum tectorum 6X, ATP Adenosine triphosphate 8X, Fumaricum acidum 8X, α-Ketoglutaricum acidum 8X, Malicum acidum 8X, Natrum oxalaceticum 8X, Pulsatilla 8X, Spongia tosta 8X, Thyreoidea suis 8X, Calcarea fuorica 10X, Funiculus umbilicalis suis 10X, Hepar suis 10X, Medulla ossis suis 10X, Splen suis 10X, Sulphur 10X, Thymus suis 10X, Cortisone aceticum 28X 22mcl each. Inactive ingredient: Sterile isotonic sodium chloride solution.

INDICATIONS AND USAGE

Thyreoidea compositum® Injection Solution is indicated for stimulation of the defense system in thyroid dysfunction, connective tissue dysfunction and glandular dysfunction.

DOSAGE AND ADMINISTRATION

The dosage schedules listed below can be used as a general guide for the administration of Thyreoidea compositum® Injection Solution. Thyreoidea compositum® Injection Solution shows individual differences in clinical response. Therefore, the dosage for each patient should be individualized according to the patient’s response to therapy. Adults and children 7 years and older: in acute disorders, 1 ampule per day, otherwise 1 ampule, 1 to 3 times per week IM/SC/IV/ID.Children ages 2 to 6 receive ½ the adult dosage.
Discard unused solution.
Thyreoidea compositum® Injection Solution may be administered intravenously, intramuscularly, subcutaneously, or intradermally. The required dose of Thyreoidea compositum® Injection Solution is first withdrawn from the ampule into the syringe, and the syringe is then shaken briefy. Thyreoidea compositum® Injection Solution should be administered using a narrow gauge needle (e.g. 22 to 30 gauge). Note: Parental drug products like Thyreoidea compositum® Injection Solution should be inspected visually for particulate matter and discoloration prior to administration whenever solution and container permit. Thyreoidea compositum® Injection Solution is a clear, colorless solution. Discolored solutions should be discarded.

WARNINGS AND PRECAUTIONS

If pain persists or worsens, if new symptoms occur, or if redness or swelling is present, the patient should be carefully re-evaluated because these could be signs of a serious condition.

Pregnancy Category C. Animal reproduction studies have not been conducted with this drug. It is also not known whether this drug can cause fetal harm when administered to a pregnant woman or can affect reproduction capacity. This drug should be given to a pregnant woman only if clearly needed.
To report SUSPECTED ADVERSE REACTIONS, contact Heel Inc. at 1.800.920.9203 or info@heelusa.com or FDA at 1-800-FDA-1088 or www.fda.gov/medwatch

OVERDOASGE

Due to the low concentration of active ingredients in homeopathic preparations such as Thyreoidea compositum® Injection Solution, adverse reactions following overdosage are extremely unlikely. However care must be taken not to exceed the recommended dosage.

CLINICAL PHARMACOLOGY

The exact mechanism of action of Thyreoidea compositum®Injection Solution is not fully understood.

PACKAGE LABEL

ThyreoideaComp_Inj_Box.jpg